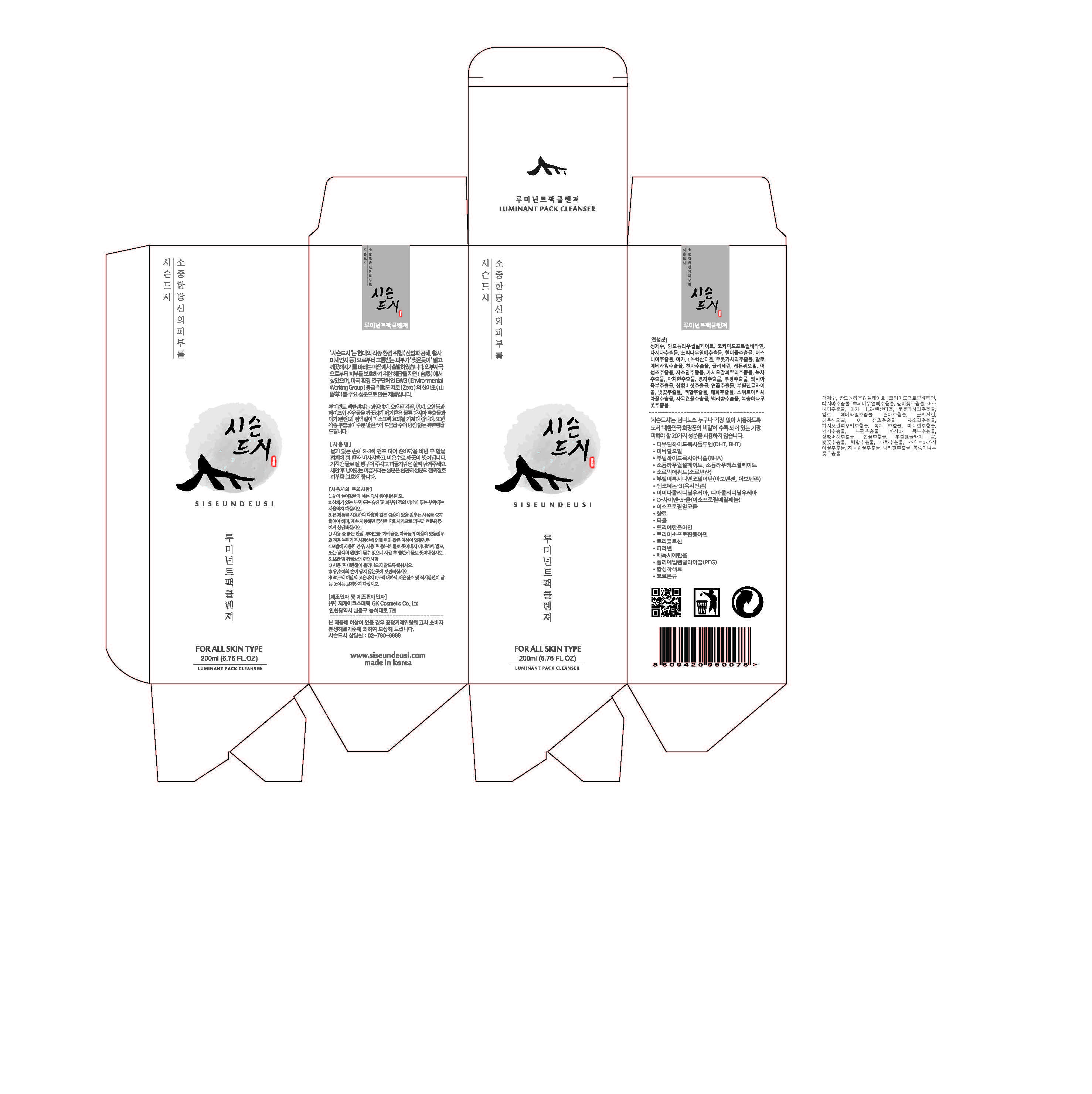 DRUG LABEL: SISEUNDEUSI LUMINANT PACK CLEANSER
NDC: 70098-0008 | Form: GEL
Manufacturer: GK COSMETIC CO., LTD.
Category: otc | Type: HUMAN OTC DRUG LABEL
Date: 20170308

ACTIVE INGREDIENTS: GLYCERIN 0.02 g/100 mL
INACTIVE INGREDIENTS: BUTYLENE GLYCOL; ALOE VERA LEAF

Drug Facts

ACTIVE INGREDIENT

Glycerin

INACTIVE INGREDIENT

Aloe Barbadensis Leaf Extract, Butylene Glycol, Etc

PURPOSE

Skin Protectant

INDICATIONS AND USAGE

Pump the Cleanser 2 to 3 times on your wet hand, rub your two hands together and gently massage your face with your hands; then rinse it all off with lukewarm water. Rinse bubbles off but don’t wash its smoothness all off because the ingredient that causes this smoothness is mucilage (which is an ingredient for natural face pack); and it protects your skin.

keep out of reach of the children

DOSAGE AND ADMINISTRATION

for external use only

WARNINGS

1. Do not use in the following cases(Eczema and scalp wounds)
2.Side Effects
1)Due to the use of this druf if rash, irritation, itching and symptopms of hypersnesitivity occur dicontinue use and consult your phamacisr or doctor
3.General Precautions
1)If in contact with the eyes, wash out thoroughty with water If the symptoms are servere, seek medical advice immediately
2)This product is for exeternal use only. Do not use for internal use
4.Storage and handling precautions
1)If possible, avoid direct sunlight and store in cool and area of low humidity
2)In order to maintain the quality of the product and avoid misuse
3)Avoid placing the product near fire and store out in reach of children